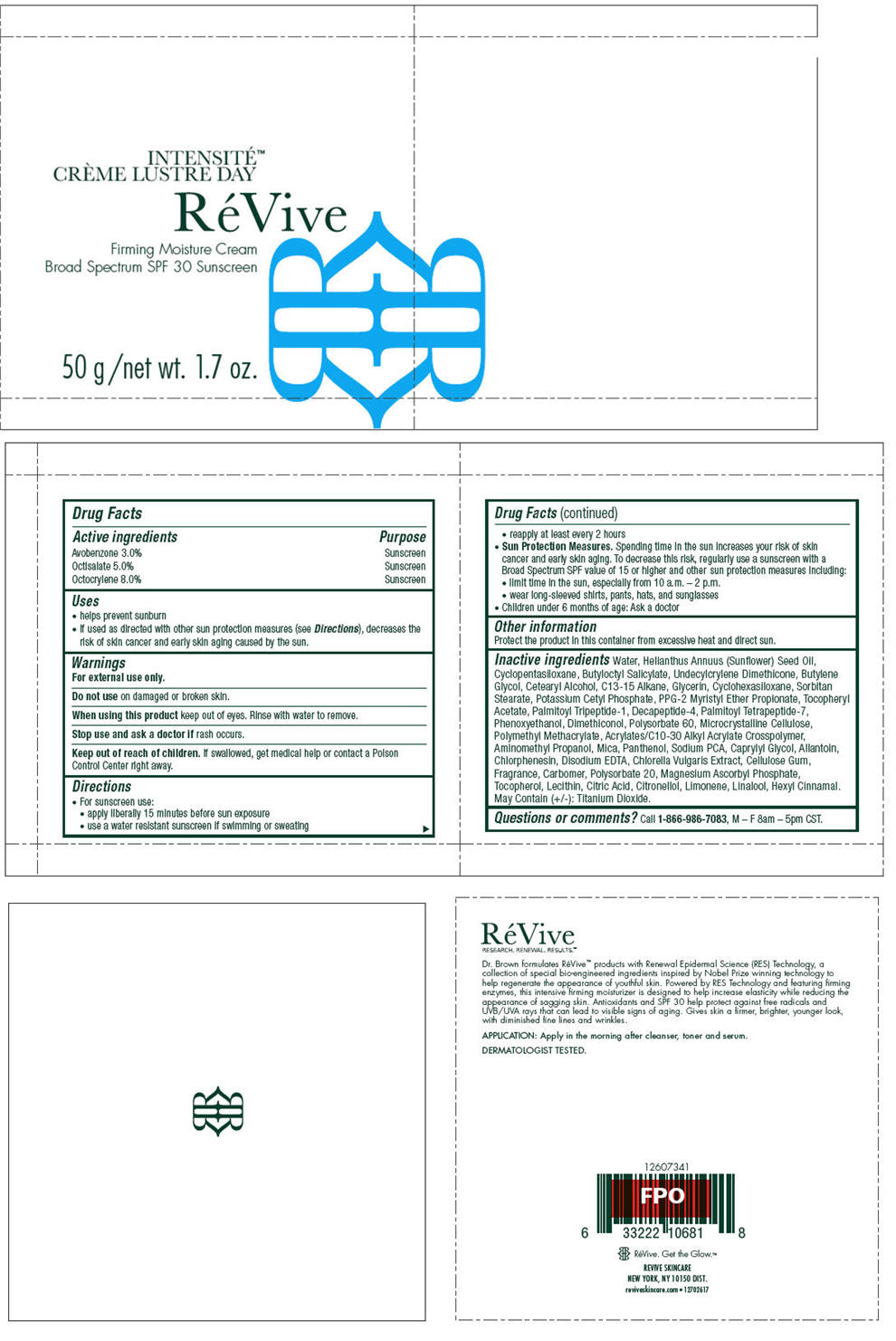 DRUG LABEL: REVIVE INTENSITE CREME LUSTRE DAY 
NDC: 58411-367 | Form: LOTION
Manufacturer: Revive Skincare
Category: otc | Type: HUMAN OTC DRUG LABEL
Date: 20171227

ACTIVE INGREDIENTS: Avobenzone 1500 mg/50 g; Octisalate 2500 mg/50 g; Octocrylene 4000 mg/50 g
INACTIVE INGREDIENTS: WATER; SUNFLOWER OIL; BUTYLOCTYL SALICYLATE; UNDECYLCRYLENE DIMETHICONE (10000 MW); BUTYLENE GLYCOL; CETOSTEARYL ALCOHOL; C13-15 ALKANE; GLYCERIN; CYCLOMETHICONE 6; SORBITAN MONOSTEARATE; POTASSIUM CETYL PHOSPHATE; PPG-2 MYRISTYL ETHER PROPIONATE; .ALPHA.-TOCOPHEROL ACETATE; PALMITOYL TRIPEPTIDE-1; PALMITOYL TETRAPEPTIDE-7; PHENOXYETHANOL; POLYSORBATE 60; MICROCRYSTALLINE CELLULOSE; POLY(METHYL METHACRYLATE; 450000 MW); CARBOMER INTERPOLYMER TYPE A (ALLYL SUCROSE CROSSLINKED); AMINOMETHYLPROPANOL; MICA; PANTHENOL; SODIUM PYRROLIDONE CARBOXYLATE; CAPRYLYL GLYCOL; ALLANTOIN; CHLORPHENESIN; EDETATE DISODIUM ANHYDROUS; CHLORELLA VULGARIS; CARBOXYMETHYLCELLULOSE SODIUM, UNSPECIFIED FORM; POLYSORBATE 20; MAGNESIUM ASCORBYL PHOSPHATE; TOCOPHEROL; CITRIC ACID MONOHYDRATE; LIMONENE, (+)-; LINALOOL, (+/-)-; TITANIUM DIOXIDE

RÉVIVE INTENSITÉ CRÈME LUSTRE DAY
Firming Moisture Cream Broad Spectrum SPF 30 Sunscreen

Drug Facts

ACTIVE INGREDIENT

Active ingredients | Purpose
Avobenzone 3.0% | Sunscreen
Octisalate 5.0% | Sunscreen
Octocrylene 8.0% | Sunscreen

Uses

- helps prevent sunburn
- if used as directed with other sun protection measures (see Directions), decreases the risk of skin cancer and early skin aging caused by the sun.

Warnings

For external use only.

Do not use on damaged or broken skin.

When using this product keep out of eyes. Rinse with water to remove.

Stop use and ask a doctor if rash occurs.

Keep out of reach of children. If swallowed, get medical help or contact a Poison Control Center right away.

Directions

- For sunscreen use:
  - apply liberally 15 minutes before sun exposure
  - use a water resistant sunscreen if swimming or sweating
  - reapply at least every 2 hours
- Sun Protection Measures. Spending time in the sun increases your risk of skin cancer and early skin aging. To decrease this risk, regularly use a sunscreen with a Broad Spectrum SPF value of 15 or higher and other sun protection measures including:
  - limit time in the sun, especially from 10 a.m. – 2 p.m.
  - wear long-sleeved shirts, pants, hats, and sunglasses
- Children under 6 months of age: Ask a doctor

Other information

Protect the product in this container from excessive heat and direct sun.

Inactive ingredients

Water, Helianthus Annuus (Sunflower) Seed Oil, Cyclopentasiloxane, Butyloctyl Salicylate, Undecylcrylene Dimethicone, Butylene Glycol, Cetearyl Alcohol, C13-15 Alkane, Glycerin, Cyclohexasiloxane, Sorbitan Stearate, Potassium Cetyl Phosphate, PPG-2 Myristyl Ether Propionate, Tocopheryl Acetate, Palmitoyl Tripeptide-1, Decapeptide-4, Palmitoyl Tetrapeptide-7, Phenoxyethanol, Dimethiconol, Polysorbate 60, Microcrystalline Cellulose, Polymethyl Methacrylate, Acrylates/C10-30 Alkyl Acrylate Crosspolymer, Aminomethyl Propanol, Mica, Panthenol, Sodium PCA, Caprylyl Glycol, Allantoin, Chlorphenesin, Disodium EDTA, Chlorella Vulgaris Extract, Cellulose Gum, Fragrance, Carbomer, Polysorbate 20, Magnesium Ascorbyl Phosphate, Tocopherol, Lecithin, Citric Acid, Citronellol, Limonene, Linalool, Hexyl Cinnamal. May Contain (+/-): Titanium Dioxide.

Questions or comments?

Call 1-866-986-7083, M – F 8am – 5pm CST.

PRINCIPAL DISPLAY PANEL - 50 g Jar Carton

INTENSITÉ™
CRÈME LUSTRE DAY

RéVive

Firming Moisture Cream
Broad Spectrum SPF 30 Sunscreen

50 g /net wt. 1.7 oz.